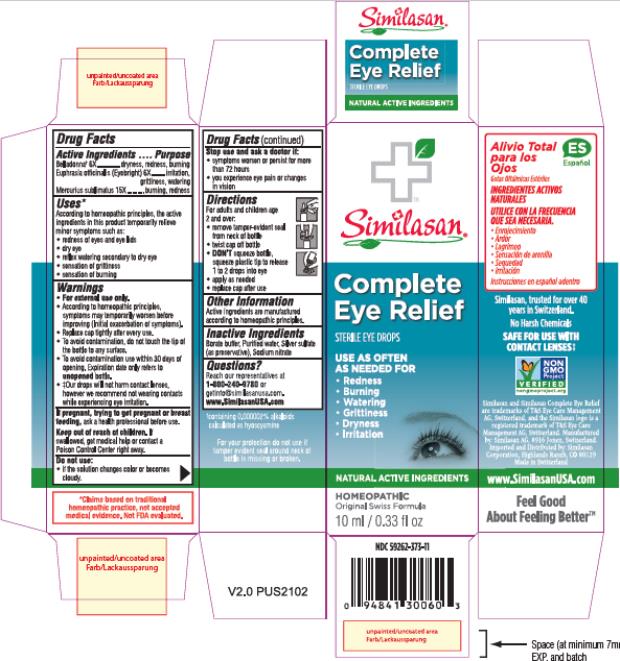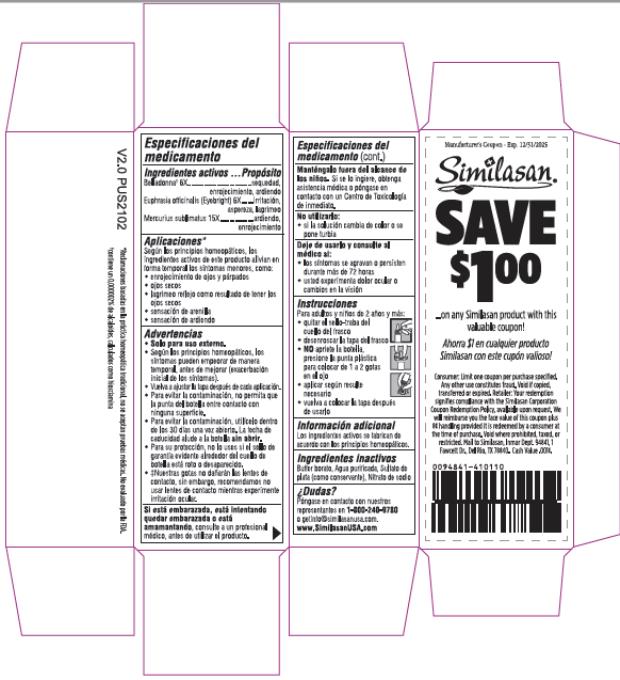 DRUG LABEL: Complete Eye Relief
NDC: 59262-373 | Form: SOLUTION/ DROPS
Manufacturer: Similasan Corporation
Category: homeopathic | Type: HUMAN OTC DRUG LABEL
Date: 20210503

ACTIVE INGREDIENTS: ATROPA BELLADONNA 6 [hp_X]/10 mL; EUPHRASIA STRICTA 6 [hp_X]/10 mL; MERCURIC CHLORIDE 15 [hp_X]/10 mL
INACTIVE INGREDIENTS: BORIC ACID; WATER; SILVER SULFATE; SODIUM NITRATE

Complete Eye Relief, 10ml

Drug Facts

Active Ingredients

Belladonna† 6X

Euphrasia officinalis (Eyebright) 6X

Mercurius sublimatus 15X

Purpose

dryness, redness, burning

irritation, grittiness, watering

burning, redness

Uses*

According to homeopathic principles, the active ingredients in this product temporarily relieve minor symptoms such as:

• redness of eyes and eye lids

• dry eye

• reflex watering secondary to dry eye

• sensation of grittiness

• sensation of burning

Warnings

• For external use only.

• According to homeopathic principles, symptoms may temporarily worsen before improving (Initial exacerbation of symptoms).

• Replace cap tightly after every use.

• To avoid contamination, do not touch the tip of the bottle to any surface.

• To avoid contamination use within 30 days of opening. Expiration date only refers to unopened bottle.

• ‡Our drops will not harm contact lenses, however we recommend not wearing contacts while experiencing eye irritation.

If pregnant, trying to get pregnant or breast feeding,

ask a health professional before use.

Keep out of reach of children.

If swallowed, get medical help or contact a Poison Control Center right away.

Do not use:

• if the solution changes color or becomes cloudy.

Stop use and ask a doctor if:

• symptoms worsen or persist for more than 72 hours

• you experience eye pain or changes in vision

Directions

For adults and children age 2 and over:

• remove tamper-evident seal from neck of bottle

• twist cap off bottle

• DON'T squeeze bottle, squeeze plastic tip to release 1 to 2 drops into eye

• apply as needed

• replace cap after use

Other Information

Active ingredients are manufactured according to homeopathic principles.

Inactive Ingredients

Borate buffer, Purified water, Silver sulfate (as preservative), Sodium nitrate

Questions?

Reach our representatives at 1-800-240-9780 or getinfo@similasanusa.com.

www.SimilasanUSA.com

†containing 0.000002% alkaloids calculated as hyoscyamine

PRINCIPAL DISPLAY PANEL

Complete
Eye Relief
STERILE
EYE DROPS
10 ml/ 0.33 fl oz